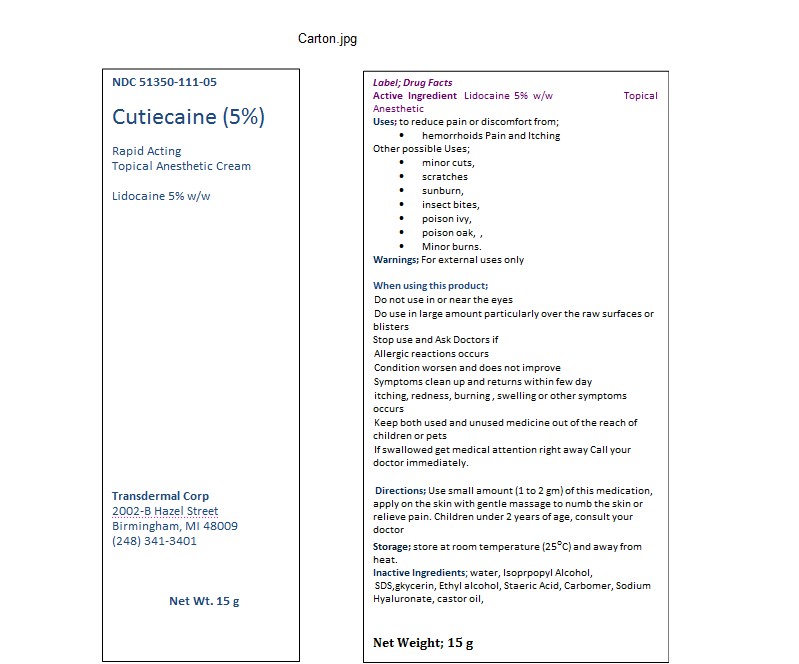 DRUG LABEL: Cutiecaine
NDC: 51350-111 | Form: CREAM
Manufacturer: Transdermal Corp
Category: otc | Type: HUMAN OTC DRUG LABEL
Date: 20111115

ACTIVE INGREDIENTS: LIDOCAINE HYDROCHLORIDE 50 mg/1 g
INACTIVE INGREDIENTS: WATER; CARBOMER HOMOPOLYMER TYPE C; GLYCERIN; STEARIC ACID; SODIUM LAURYL SULFATE; ISOPROPYL ALCOHOL; CETYL ALCOHOL; ALCOHOL; ALOE ; HYALURONATE SODIUM; POLYSORBATE 20; BUTYLENE GLYCOL; CASTOR OIL

Drug Facts

ACTIVE INGREDIENT

Cutiecaine-5%, Topical Lidocaine Cream (5% w/w),Active Ingredient; Lidocaine Hydrochloride 4% (w/w), Inactive Ingredients; water, Isoprpopyl Alcohol, gkycerin, Ethyl alcohol, Staeric Acid, Carbomer, Sodium Hyaluronate, castor oil,Innovatech Inc, Net Wt. 15g

PURPOSE

for relief of pain and discomfort from; hemorrhoids pain and Itching, Other Uses; minor cuts, bruises, sun burn, insect bites, poison ivy, etc.

INDICATIONS AND USAGE

Use for reducing pain or discomfort from; hemorrhoids pain and Itching. minor cuts, abrasions, minor burns, sun burns, insect bites, poison ivy, Use small amount (1 to 2 gm) of this medication, apply on the skin with gentle massage to numb the skin or relieve pain (do not occlude). Children under 2 years of age, consult your doctor

KEEP OUT OF REACH OF CHILDREN

Keep both used and unused medicine out of the reach of children or pets

INACTIVE INGREDIENT

Inactive Ingredients; water, Isoprpopyl Alcohol, gkycerin, Ethyl alcohol, Staeric Acid, Carbomer, Sodium Hyaluronate, castor oil,SDS, Net Wt. 15g

DOSAGE AND ADMINISTRATION

Use for reducing pain or discomfort from minor cuts, abrasions, minor burns, sun burns, insect bites, poison ivy, hemorrhoids pain and Itching. Use small amount (1 to 2 gm) of this medication, apply on the skin with gentle massage to numb the skin or relieve pain (do not occlude). Children under 2 years of age, consult your doctor

• Do not use in or near the eyes
• Do use in large amount particularly over the raw surfaces or blisters
Stop use and Ask Doctors if
• Allergic reactions occurs
• Condition worsen and does not improve
• Symptoms clean up and returns within few day
• itching, redness, burning , swelling or other symptoms occurs
• Keep both used and unused medicine out of the reach of children or pets
• If swallowed get medical attention right away Call your doctor immediately.

PACKAGE LABEL

carton.jpg